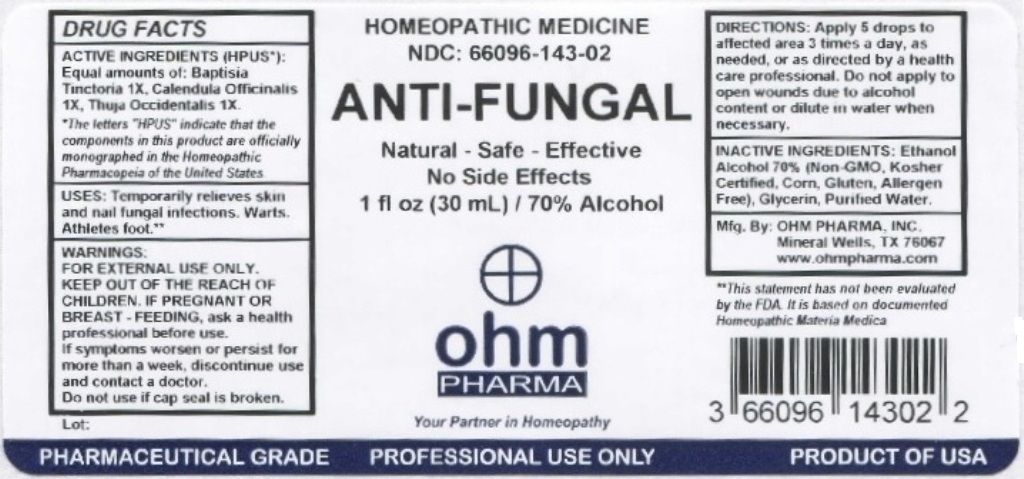 DRUG LABEL: Anti Fungal
NDC: 66096-143 | Form: LIQUID
Manufacturer: OHM PHARMA INC.
Category: homeopathic | Type: HUMAN OTC DRUG LABEL
Date: 20211229

ACTIVE INGREDIENTS: BAPTISIA TINCTORIA ROOT 1 [hp_X]/30 mL; CALENDULA OFFICINALIS FLOWERING TOP 1 [hp_X]/30 mL; THUJA OCCIDENTALIS LEAFY TWIG 1 [hp_X]/30 mL
INACTIVE INGREDIENTS: ALCOHOL; GLYCERIN; WATER

OHM Anti-Fungal

ACTIVE INGREDIENT

AVTIVE INGREDIENTS (HPUS*): Equal amounts of: Baptisia Tinctoria 1X, Calendula Officinalis 1X, Thuja Occidentalis 1X.

*The letters "HPUS" indicate that the components in this product are officially monographed in the Homeopathic Pharmacopeia of the United States.

INDICATIONS AND USAGE

USES: Temporarily relieves skin and nail fungal infections. Warts, Athletes foot.**

**This statement has not been evaluated by the FDA. It is based on documented Homeopathic Materia Medica.

WARNINGS

WARNINGS: FOR EXTERNAL USE ONLY.IF PREGNANT OR BREAST-FEEDING, ask a health professional before use. If symptoms worsen or persist for more than a week, discontinue use and contact a doctor.

- KEEP OUT OF REACH OF CHILDREN.

DOSAGE AND ADMINISTRATION

DIRECTIONS: Apply 5 drops to affected area 3 times a day, as needed, or as directed by a health care professional. Do not apply to open wounds due to alcohol content or dilute in water when necessary.

Do not use if cap seal is broken.

INACTIVE INGREDIENT

INACTIVE INGREDIENTS: Ethanol Alcohol 70% (Non GMO, Kosher Certified, Corn, Gluten, Allergen Free), Glycerin, Purified Water.

QUESTIONS

Mfg. By: OHM PHARMA, INC. Mineral Wells, TX 76067

www.ohmpharma.com

PACKAGE LABEL

HOMEOPATHIC MEDICINE

NDC: 66096-143-02

ANTI-FUNGAL

Natural - Safe - Effective

No Side Effects

1 fl oz (30mL) / 70% Alcohol

PRODUCT OF USA

PURPOSE

Temporarily relieves skin and nail fungal infections.